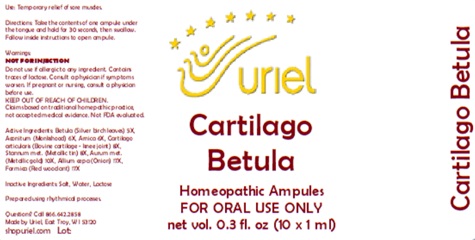 DRUG LABEL: Cartilago Betula
NDC: 48951-3039 | Form: LIQUID
Manufacturer: Uriel Pharmacy Inc.
Category: homeopathic | Type: HUMAN OTC DRUG LABEL
Date: 20251126

ACTIVE INGREDIENTS: BETULA PUBESCENS LEAF 5 [hp_X]/1 mL; ACONITUM NAPELLUS 6 [hp_X]/1 mL; ARNICA MONTANA 6 [hp_X]/1 mL; BOS TAURUS CARTILAGE 8 [hp_X]/1 mL; TIN 8 [hp_X]/1 mL; GOLD 10 [hp_X]/1 mL; ONION 17 [hp_X]/1 mL; FORMICA RUFA 17 [hp_X]/1 mL
INACTIVE INGREDIENTS: WATER; SODIUM CHLORIDE; LACTOSE, UNSPECIFIED FORM

Cartilago Betula

PURPOSE

Use: Temporary relief of sore muscles.

INDICATIONS AND USAGE

FOR ORAL USE ONLY

DOSAGE AND ADMINISTRATION

Directions: Take the contents of one ampule under the tongue and hold for 30 seconds, then swallow. Follow inside instructions to open ampule.

Warnings:
NOT FOR INJECTION
Do not use if allergic to any ingredient. Contains traces of lactose. Consult a physician if symptoms worsen. If pregnant or nursing, consult a physician before use.
Claims based on traditional homepathic practice, not accepted medical evidence. Not FDA evaluated.

KEEP OUT OF REACH OF CHILDREN.

ACTIVE INGREDIENT

Active Ingredients: Betula (Silver birch leaves) 5X, Aconitum (Monkshood) 6X, Arnica 6X, Cartilago articularis (Bovine cartilage - knee joint) 8X, Stannum met. (Metallic tin) 8X, Aurum met. (Metallic gold) 10X, Allium cepa (Onion) 17X, Formica (Red wood ant) 17X

Inactive Ingredients: Water, Salt, Lactose

Prepared using rhythmical processes.

Questions? Call 866.642.2858
Made by Uriel, East Troy, WI 53120
shopuriel.com